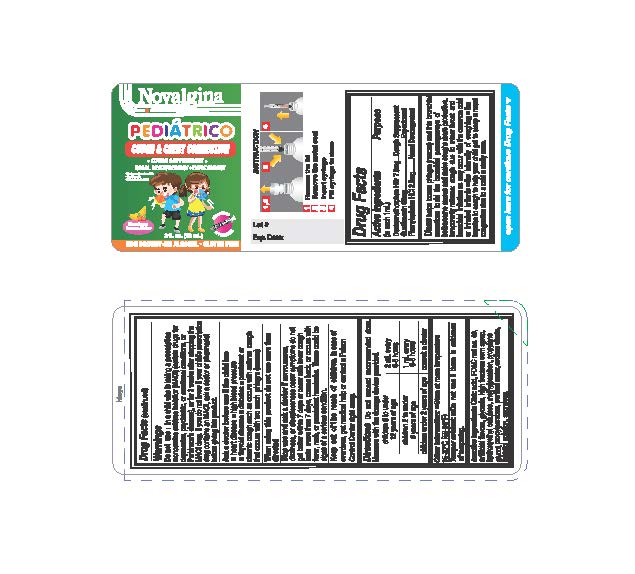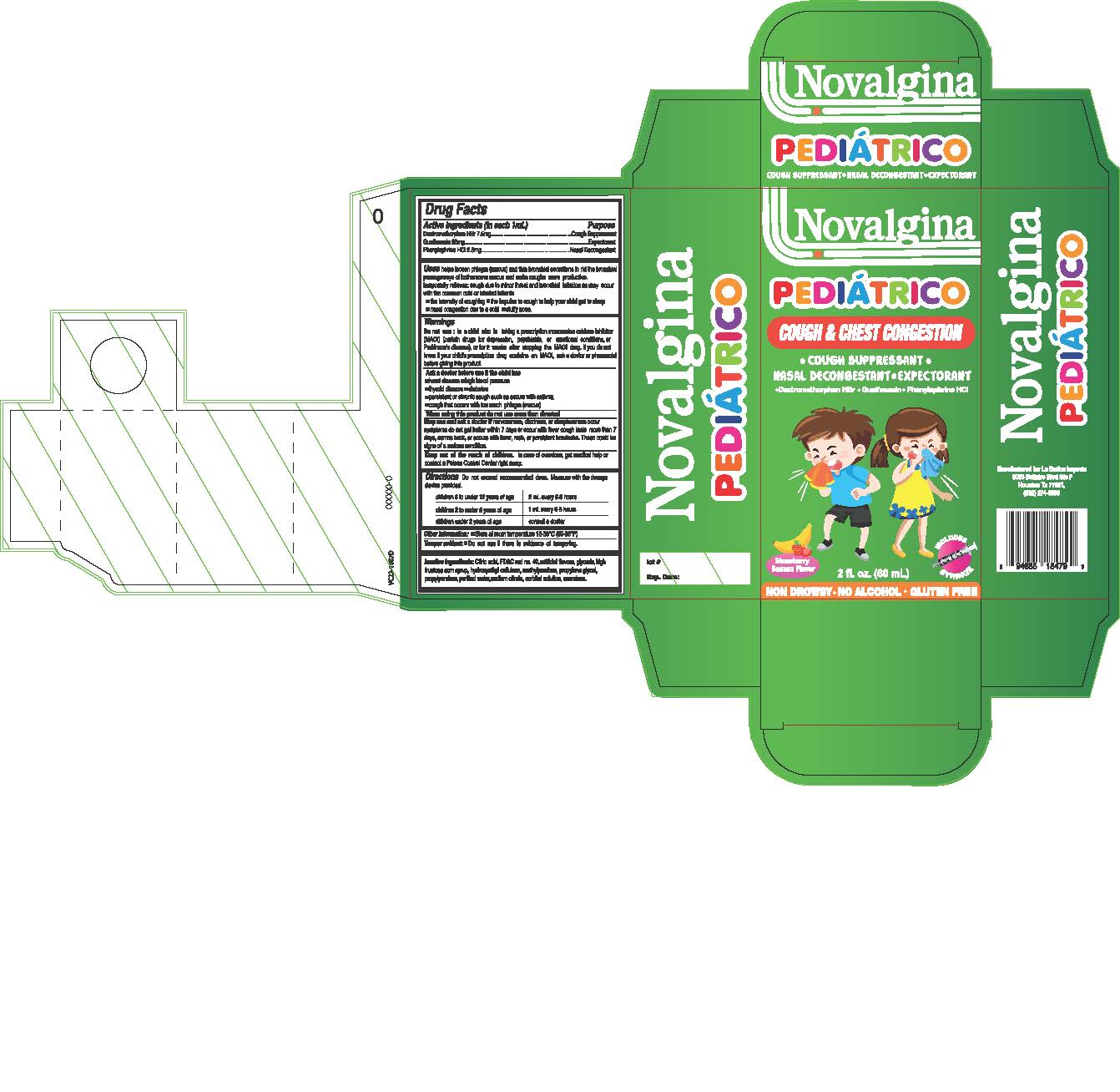 DRUG LABEL: Novalgina Pediatrico Cough and Cold
NDC: 83057-0002 | Form: LIQUID
Manufacturer: HBC Pharma LLC
Category: otc | Type: HUMAN OTC DRUG LABEL
Date: 20241104

ACTIVE INGREDIENTS: DEXTROMETHORPHAN HYDROBROMIDE 7.5 mg/1 mL; GUAIFENESIN 88 mg/1 mL; PHENYLEPHRINE HYDROCHLORIDE 2.5 mg/1 mL
INACTIVE INGREDIENTS: METHYLPARABEN; PROPYLPARABEN; FD&C RED NO. 40; GLYCERIN; CITRIC ACID MONOHYDRATE; HIGH FRUCTOSE CORN SYRUP; HYDROXYETHYL CELLULOSE (100 MPA.S AT 2%); PROPYLENE GLYCOL; WATER; SODIUM CITRATE; SORBITOL; SUCRALOSE

Novalgina Pediatrico Cough and Cold

Active Ingredients:(in each 1 ml.) | Purpose
Dextromethorphan Hydrobromide 7.5 mg ....................... | Cough Suppressant
Guaifenesin 88 mg...................................................... | Expectorant
Phenylephrine HCl 2.5 mg....................................................... | Decongestant

Uses:

- Helps loosen phlegm (mucus) and thin bronchial secretions to drain bronchial tubes and make the cough more productive.
- Temporarily relieves cough due to minor throat and bronchial irritation as may occur with the common cold. or inhaled irritants
- the intensity of coughing
- The impulse to cough to help your child get to sleep
- nasal congestion due to a cold
- stuffy nose

Warnings

in a child who is taking prescription monoamine oxidase inhibitor (MAOI) (certain drugs for depression, psychiatric, or emotional conditions, or Parkinson's disease), or for 2 weeks after stopping the MAOI drug. If you do not know if your child's prescription drug contains an MAOI, ask a doctor or pharmacist before giving this product.

Do not Use

in a child who is taking prescription monoamine oxidase inhibitor (MAOI) (certain drugs for depression, psychiatric, or emotional conditions, or Parkinson's disease), or for 2 weeks after stopping the MAOI drug. If you do not know if your child's prescription drug contains an MAOI, ask a doctor or pharmacist before giving this product.

Ask a doctor before use if the child has

- Heart disease
- high blood pressure
- thyroid disease
- diabetes
- persistent or chronic cough such as occurs with asthma
- cough that occurs with too much phlegm (mucus)

When using this product do not use more that directed

Stop use and ask a doctor

If nervousness, dizziness, or sleeplessness occur symptoms do not get better within 7 days or occur with fever cough last more than 7 days, comes back, or occurs with fever, rash, or persistent headache. These could be signs of a serious condition.

Keep out of reach of children.

In case of overdose, get medical help or contact a Poison Control Center right away.

Other Information:

Each 1 mls

Store between 15 - 30 degrees Celsius (59 - 86 Fahrenheit).

Other Information:

- Store between 15 - 30 degrees Celsius (59 - 86 Fahrenheit).
- Tamper Evident Feature: Do not use if there is evidence of tampering

Inactive Ingredient

Citric Acid, FD&C red no. 40, artificial flavors, glycerine, high fructose corn syrup, Hydroxyethyl Cellulose, methylparaben, propylene glycol, Propylparaben, purified water, sodium citrate, sorbitol solution, sucralose.

Dosage and Administration

Do not exceed recommended dose. Measure with the dosage device provided

Children 6 to under 12 years of age 2 ml every 6-8 hours
Children 2 to under 6 years of age 1 ml every 6-8 hours
Children under 2 years of age Consult a doctor